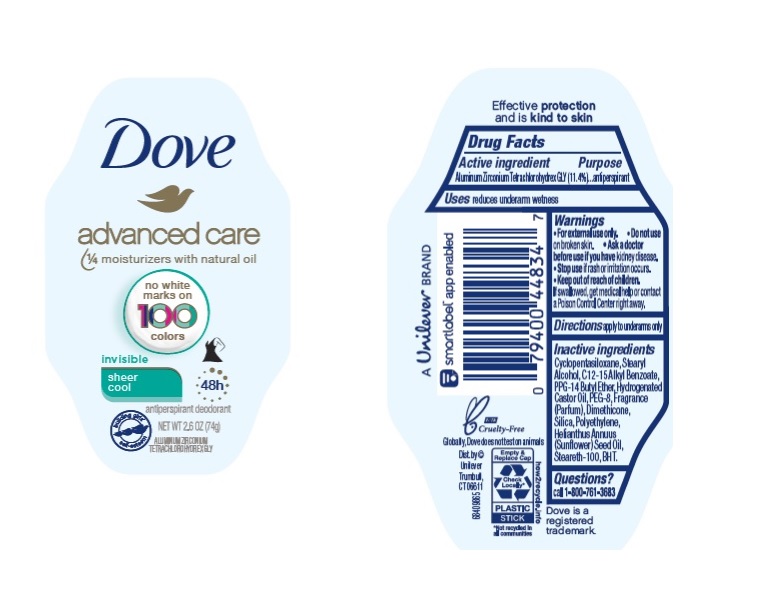 DRUG LABEL: Dove
NDC: 64942-1816 | Form: STICK
Manufacturer: Conopco, Inc. d/b/a/ Unilever
Category: otc | Type: HUMAN OTC DRUG LABEL
Date: 20241110

ACTIVE INGREDIENTS: ALUMINUM ZIRCONIUM TETRACHLOROHYDREX GLY 11.4 g/100 g
INACTIVE INGREDIENTS: CYCLOMETHICONE 5; STEARYL ALCOHOL; ALKYL (C12-15) BENZOATE; PPG-14 BUTYL ETHER; HYDROGENATED CASTOR OIL; POLYETHYLENE GLYCOL 400; DIMETHICONE; SILICON DIOXIDE; HIGH DENSITY POLYETHYLENE; SUNFLOWER OIL; STEARETH-100; BUTYLATED HYDROXYTOLUENE

Dove Advanced Care Invisible Sheer Cool 48h Antiperspirant Deodorant

DOVE ADVANCED CARE SHEER COOL 48H ANTIPERSPIRANT DEODORANT - aluminum zirconium tetrachlorohydrex gly stick

Dove Advanced Care Invisible Sheer Cool 48h Antiperspirant Deodorant

Active ingredient

Aluminum Zirconium Tetrachlorohydrex GLY (11.4%)

Purpose

antiperspirant

Uses

• reduces underarm wetness

Warnings

• For external use only
• Do not use on broken skin
• Ask a doctor before use if you have kidney disease
• Stop use if rash or irritation occurs

• Keep out of reach of children. If swallowed, get medical help or contact a Poison Control Center right away.

Directions

apply to underarms only

Inactive ingredients

Cyclopentasiloxane, Stearyl Alcohol, C12-15 Alkyl Benzoate, PPG-14 Butyl Ether, Hydrogenated Castor Oil, PEG-8, Fragrance (Parfum), Dimethicone, Silica, Polyethylene, Helianthus Annuus (Sunflower) Seed Oil, Steareth-100, BHT.

Questions?

Call toll-free 1-800-761-3683